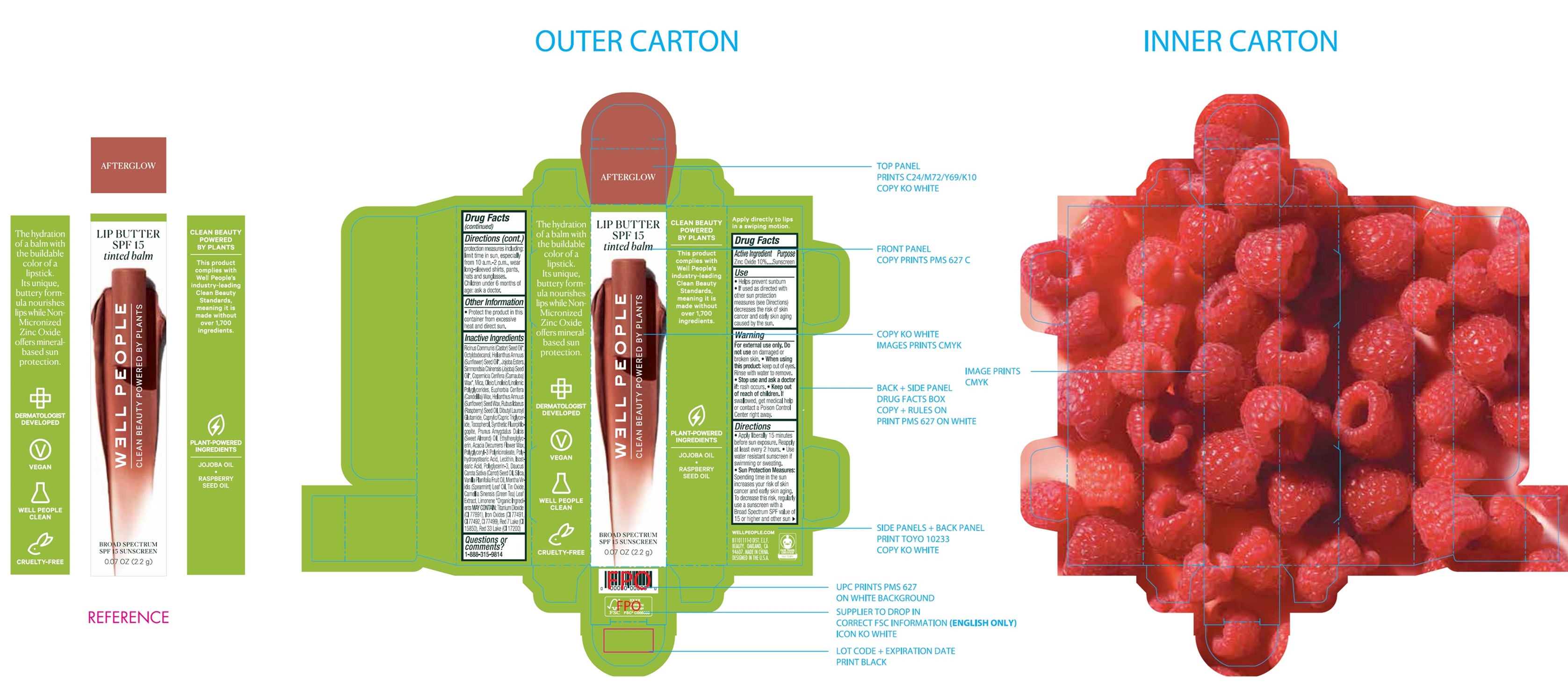 DRUG LABEL: Well People Lip Butter SPF 15 Sunscreen AFTERGLOW
NDC: 76354-493 | Form: CREAM
Manufacturer: e.l.f. Cosmetics, Inc
Category: otc | Type: HUMAN OTC DRUG LABEL
Date: 20251107

ACTIVE INGREDIENTS: ZINC OXIDE 100 mg/1 g
INACTIVE INGREDIENTS: CASTOR OIL; OCTYLDODECANOL; HELIANTHUS ANNUUS FLOWERING TOP; JOJOBA OIL; CARNAUBA WAX; MICA; CANDELILLA WAX; HELIANTHUS ANNUUS SEED WAX; RASPBERRY SEED OIL; DIBUTYL LAUROYL GLUTAMIDE; MEDIUM-CHAIN TRIGLYCERIDES; TOCOPHEROL; ALMOND OIL; ETHYLHEXYLGLYCERIN; ACACIA DECURRENS FLOWER WAX; ISOSTEARIC ACID; POLYGLYCERIN-3; CARROT SEED OIL; SILICON DIOXIDE; VANILLA PLANIFOLIA OIL; SPEARMINT OIL; STANNIC OXIDE; GREEN TEA LEAF; LIMONENE, (+)-

Well People Lip Butter SPF 15 Sunscreen AFTERGLOW

Active Ingredient

Zinc Oxide 10%

Purpose

Sunscreen

Use

- Helps prevent sunburn
- If used as directed with other sun protection measures (see Directions) decreases the risk of skin cancer and early skin aging caused by the sun.

Warning

For external use only.

Do not use

on damaged or broken skin.

When using this product:

- keep out of eyes. Rinse with water to remove.

Stop use and ask a doctor if:

- rash occurs.

Keep out of reach of children.

- If swallowed, get medical help or contact a Poison Control Center right away.

Directions

- Apply liberally 15 minutes before sun exposure. Reapply at least every 2 hours.
- Use water resistant sunscreen if swimming or sweating.
- Sun Protection Measures:Spending time in the sun increases your risk of skin cancer and early skin aging. To decrease this risk, regularly use a sunscreen with a Broad Spectrum SPF value of 15 or higher and other sun protection measures including:limit time in sun, especially from 10 a.m.-2 p.m., wear long-sleeved shirts, pants, hats and sunglasses. Children under 6 months of age: ask a doctor.

Other Information

- Protect the product in this container from excessive heat and direct sun.

Inactive Ingredients

Ricinus Communis (Castor) Seed Oil*, Octyldodecanol, Heliathus Annuus (Sunflower) Seed Oil*, Jojoba Esters, Simmondsia Chinensis (Jojoba) Seed Oil* Copernicia Cerifera (Carnauba) Wax*, Mica, Oleic/Linoleic/Linolenic Polyglycerides, Euphorbia Cerifera (Candelilla) Wax, Helianthus Annuus (Sunflower) Seed Wax, Rubus Idaeus (Raspberry) Seed Oil, Dibutyl Lauroyl Glutamide, Caprylic/Capric Triglyceride, Tocopherol, Synthetic Fluorphlogopite, Prunus Amygdalus Dulcis (Sweet Almond) Oil, Ethylhexylglycerin, Acacia Decurrens Flower Wax, Polyglyceryl-3 Polyricinoleate, Polyhydroxystearic Acid, Lecithin, Isostearic Acid, Polyglycerin-3, Daucus Carota Sativa (Carrot) Seed Oil, Silica, Vanilla Planifolia Fruit Oil, Mentha Viridis (Spearmint) Leaf Oil, Tin Oxide, Camellia Sinensis (Green Tea) Leaf Extract, Limonene *Orgainc Ingredients MAY CONTAIN:Titanium Dioxide (CI 77891), Iron Oxides (CI 77491, CI 77492, CI 77499), Red 7 Lake (CI 15850), Red 33 Lake (CI 17200)

Questions or comments?

1-888-315-9814